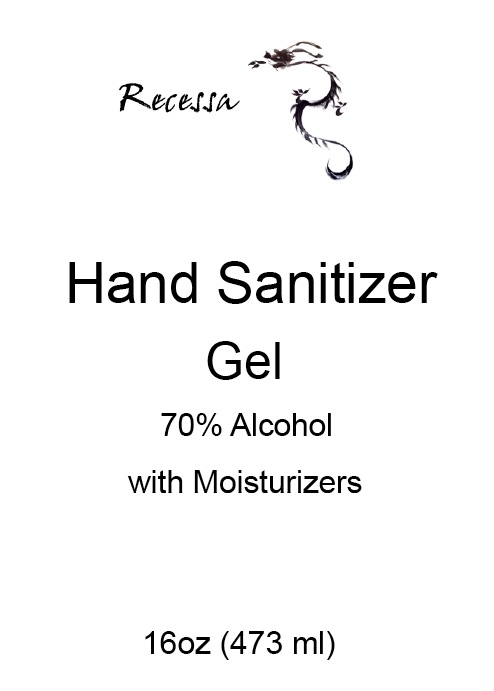 DRUG LABEL: Recessa Hand Sanitizer
NDC: 70420-001 | Form: GEL
Manufacturer: Specialty Formulations
Category: otc | Type: HUMAN OTC DRUG LABEL
Date: 20210120

ACTIVE INGREDIENTS: ALCOHOL 70 mL/100 mL
INACTIVE INGREDIENTS: WATER; TROLAMINE; WITCH HAZEL; GLYCERIN; ALOE VERA LEAF; .ALPHA.-TOCOPHEROL ACETATE; CARBOMER 940

Recessa Hand Sanitizer Gel
70% Alcohol

Active Ingredient

Ethyl Alcohol 70% v/v

Purpose

Antiseptic

Uses

to reduce disease causing bacteria
on the skin when soap and water not
available

Warnings

For external use only.
Flammable. Keep away from heat or
flame

When using this product

■ Keep out of eyes,
ears, and mouth. In case of contact with
eyes, rinse eyes thoroughly with water.

Do not use:

■ on open skin wounds

■ in children less than 2 months of age

Stop use and ask a doctor if:

Skin irritation or rash develop

Keep out of reach of children. If swallowed,
seek medical help or contact Poison Control
Center right away

Directions:

Place enough product on hands
to cover all surfaces. Rub hands together
until dry. ■ for children under 6, use only
under adult supervision

Other Information:

■ Store between 15°- 30°C (59°- 86° F)
■ Avoid freezing and excessive heat
above 40°C (104°F

Inactive Ingredients:

Aloe Vera Gel,
Carbomer, Glycerin, Vitamin E, Purified
Water, Triethanolamine and Witch Hazel

Package Label - Principal Display Panel

Recessa

Hand Sanitizer

Gel

70% Alcohol

with Moisturizers

16oz (473 ml)